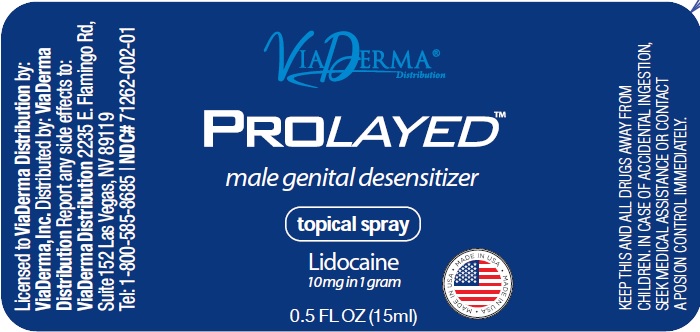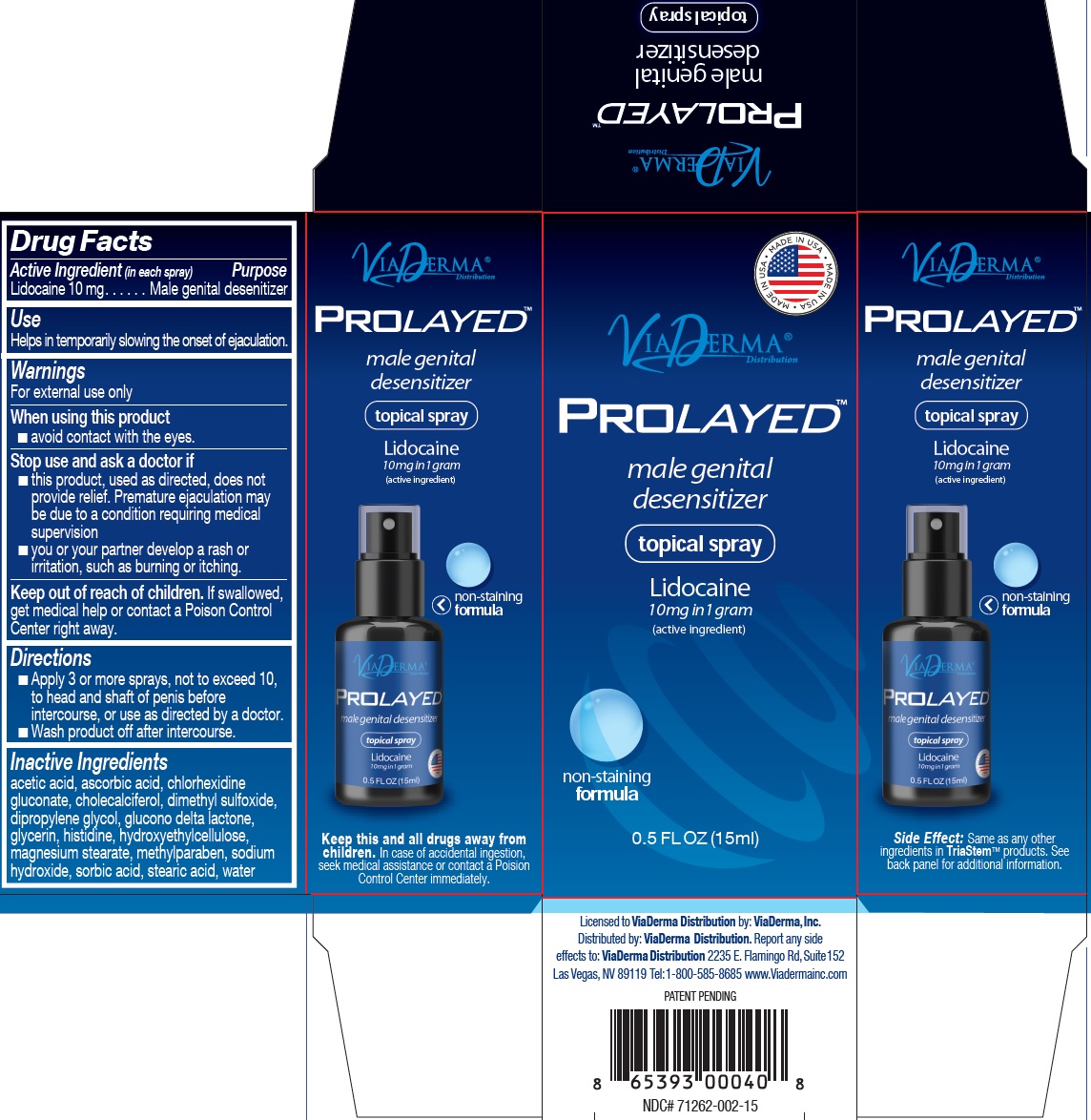 DRUG LABEL: Prolayed Lidocaine Male Genital Desensitizer
NDC: 71262-006 | Form: OINTMENT
Manufacturer: ViaDerma Distribution, Inc.
Category: otc | Type: HUMAN OTC DRUG LABEL
Date: 20231202

ACTIVE INGREDIENTS: LIDOCAINE 10 mg/1 mL
INACTIVE INGREDIENTS: SORBIC ACID; ACETIC ACID; ASCORBIC ACID; CHLORHEXIDINE GLUCONATE; CHOLECALCIFEROL; DIMETHYL SULFOXIDE; DIPROPYLENE GLYCOL; GLUCONOLACTONE; GLYCERIN; HISTIDINE; MAGNESIUM STEARATE; METHYLPARABEN; SODIUM HYDROXIDE; STEARIC ACID; WATER

Prolayed Lidocaine Ointment-Male Genital Desensitizer

Active Ingredient

Lidocaine 10 mg

Purpose

Male genital desenitizer

Use

Helps in temporarily slowing the onset of ejaculation.

Warnings

For external use only

When using this product

- avoid contact with the eyes.

Stop use and ask a doctor if

- this product, used as directed, does not provide relief. Premature ejaculation may be due to a condition requiring medical supervision
- you or your partner develop a rash or irritation, such as burning or itching.

Keep out of reach of children.

If swallowed, get medical help or contact a Poison Control Center right away.

Directions

- Apply 3 or more sprays, not to exceed 10, to head and shaft of penis before intercourse, or use as directed by a doctor.
- Wash product off after intercourse.

Inactive Ingredients

acetic acid, ascorbic acid, chlorhexidine gluconate, cholecalciferol, dimethyl sulfoxide, dipropylene glycol, glucono delta lactone, glycerin, histidine, hydroxethyl-cellulose, magnesium stearate, methylparaben, sodium hydroxide, sorbic acid, stearic acid, water